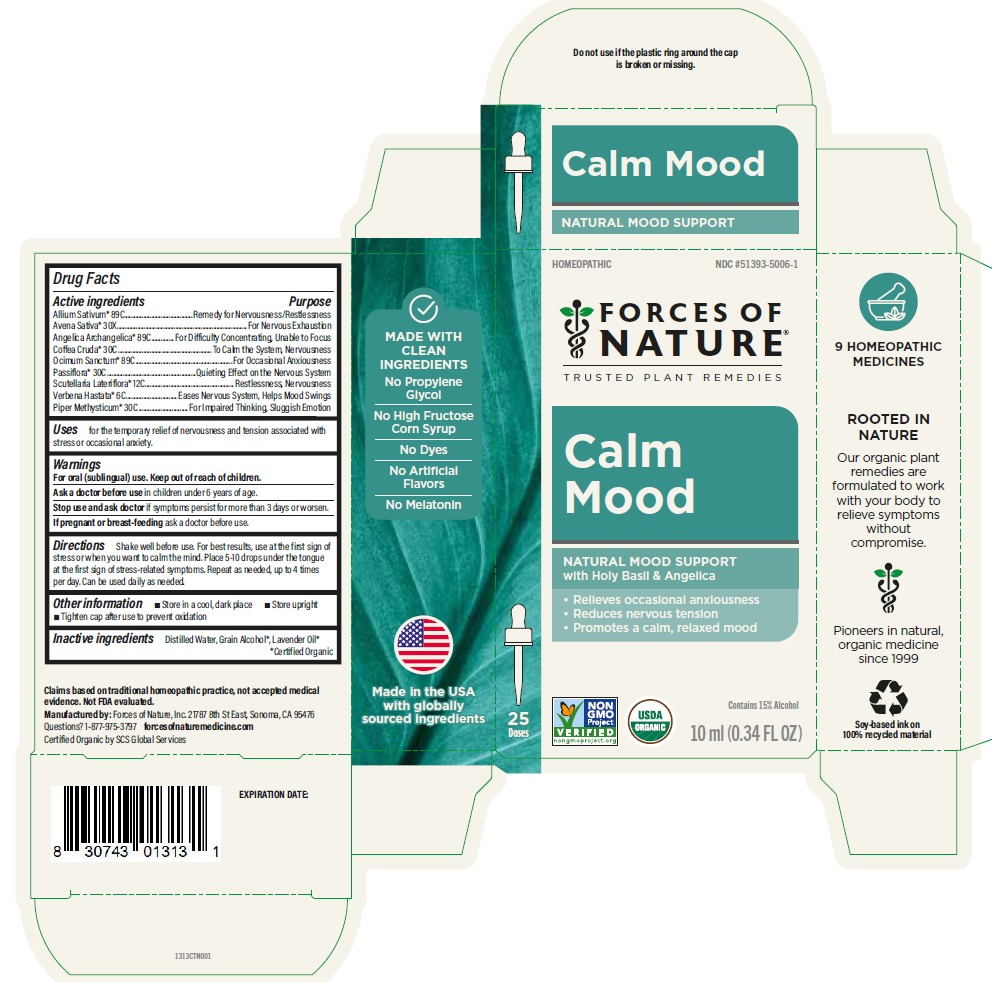 DRUG LABEL: Calm Mood
NDC: 51393-5006 | Form: SOLUTION/ DROPS
Manufacturer: Forces of Nature
Category: homeopathic | Type: HUMAN OTC DRUG LABEL
Date: 20260225

ACTIVE INGREDIENTS: GARLIC 89 [hp_C]/100 mL; AVENA SATIVA FLOWERING TOP 30 [hp_X]/100 mL; ANGELICA ARCHANGELICA ROOT 89 [hp_C]/100 mL; ARABICA COFFEE BEAN 30 [hp_C]/100 mL; HOLY BASIL LEAF 89 [hp_C]/100 mL; PASSIFLORA EDULIS FLOWER 30 [hp_C]/100 mL; SCUTELLARIA LATERIFLORA WHOLE 12 [hp_C]/100 mL; VERBENA HASTATA TOP 6 [hp_C]/100 mL; MACROPIPER METHYSTICUM ROOT 30 [hp_C]/100 mL
INACTIVE INGREDIENTS: WATER; ALCOHOL; LAVENDER OIL

Calm Mood

Drug Facts

ACTIVE INGREDIENT

Active ingredients | Purpose
Allium Sativum * [*Certified Organic] 89C | Remedy for Nervousness/Restlessness
Avena Sativa * 30X | For Nervous Exhaustion
Angelica Archangelica 89C | For Difficulty Concentrating, Unable to Focus
Coffea Cruda * 30C | To Calm the System, Nervousness
Ocimum Sanctum * 89C | For Occasional Anxiousness
Passiflora * 30C | Quieting Effect on the Nervous System
Scutellaria Lateriflora * 12C | Restlessness, Nervousness
Verbena Hastata * 6C | Eases Nervous System, Helps Mood Swings
Piper Methysticum * 30C | For Impaired Thinking, Sluggish Emotion

Uses

for the temporary relief of nervousness and tension associated with stress or occasional anxiety.

Warnings

For oral (sublingual) use.

Ask a doctor before usein children under 6 years of age.

Stop use and ask doctorif symptoms persist for more than 3 days or worsen.

PREGNANCY OR BREAST FEEDING

If pregnant or breast-feedingask a doctor before use.

Keep out of reach of children.

Directions

Shake well before use. For best results, use at the first sign of stress or when you want to calm the mind. Place 5 - 10 drops under the tongue at the first sign of stress-related symptoms, Repeat as needed, up to 4 times per day. Can be used daily as needed.

RECENT MAJOR CHANGES

Updated wording of the Directions section to reflect clearer consumer communication about this serving to temporarily relieve symptoms of occasional anxiety.

Other information

- Store in a cool, dark place
- Store upright
- Tighten cap after use to prevent oxidation

Inactive ingredients

Distilled Water, Grain Alcohol* , Lavender Oil*

Questions or comments?

Questions? 1-877-975-3797 forcesofnaturemedicine.com

Manufactured by: Forces of Nature, Inc.21787 8th St East, Sonoma, CA 95476

PRINCIPAL DISPLAY PANEL - 10 ml Bottle Carton

HOMEOPATHIC
NDC #51393-5006-1

FORCES OF NATURE®

TRUSTED PLANT REMEDIES

Calm Mood

NATURAL MOOD SUPPORT

with Holy Basil & Angelica

- Relieves occasional anxiousness
- Reduces nervous tension
- Promotes a calm, relaxed mood

NON

GMO

Project

VERIFIED

nongmoproject.org

USDA

ORGANIC

Contains 15% Alcohol

10 ml (0.34 FL OZ)